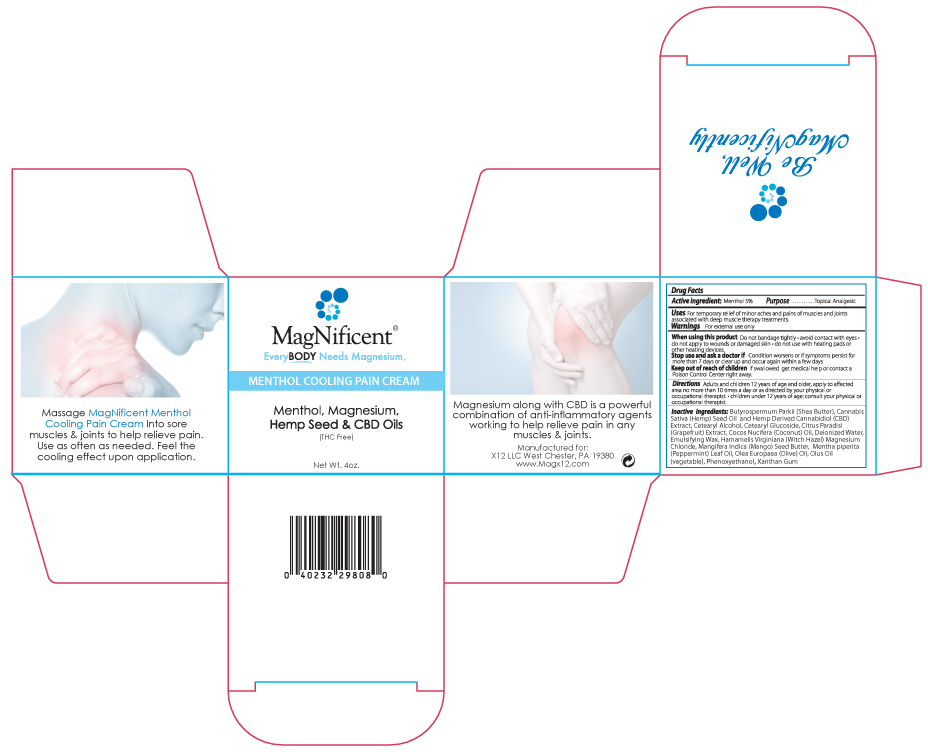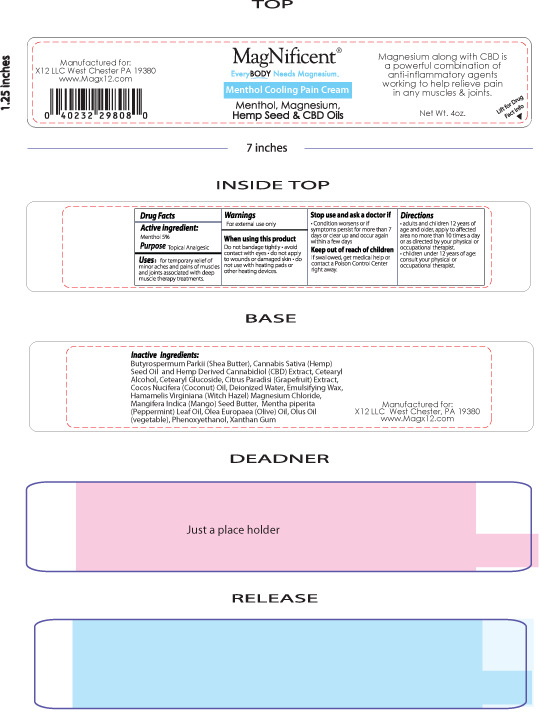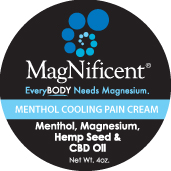 DRUG LABEL: MagNificent Menthol Cooling Pain Cream
NDC: 76348-421 | Form: CREAM
Manufacturer: Renu Laboratories, Inc.
Category: otc | Type: HUMAN OTC DRUG LABEL
Date: 20220114

ACTIVE INGREDIENTS: MENTHOL 5.6 g/112 g
INACTIVE INGREDIENTS: CANNABIS SATIVA SEED OIL; CORN OIL; MAGNESIUM CHLORIDE; MANGIFERA INDICA SEED BUTTER; LAURETH-7; SHEA BUTTER; XANTHAN GUM; WHITE WAX; WITCH HAZEL; PHENOXYETHANOL; POLYACRYLAMIDE (10000 MW); C13-14 ISOPARAFFIN; PEPPERMINT OIL; GRAPEFRUIT OIL; CANNABIDIOL; WATER; CETEARYL GLUCOSIDE; COCONUT OIL; OLIVE OIL; CETOSTEARYL ALCOHOL

MagNificent Menthol Cooling Pain Cream

Active Ingredient

Menthol 5%

Purpose

Topical Analgesic

Warnings

For external use only

When using this product

Do not bandage tightly

- avoid contact with eyes
- do not apply to wounds or damaged skin
- do not use with heating pads or other heating devices.

Stop use and ask a doctor if

Condition worsens or if symptoms persist for more than 7 days or clear up and occur again within a few days

Keep out of reach of children

If swallowed, get medical help or contact a Poison Control Center right away.

Directions

Adults and children 12 years of age and older, apply to affected area no more than 10 times a day or as directed by your physicial or occupational therapist

- children under 12 years of age: contact physical or occupational therapist

Inactive Ingredients:

Butyrospermum Parkii (Shea

Butter), Cannabis Sativa (Hemp) Seed Oil and Hemp Derived Cannabidiol

(CBD) Extract, Cetearyl Alcohol,

Cetearyl Glucoside, Citrus Paradisi (Grapefruit) Extract, Cocos Nucifera

(Coconut) Oil, Deionized Water, Emulsifying Wax,

Hamamelis Virginiana (Witch Hazel) Magnesium Chloride,

Mangifera Indica (Mango) Seed Butter,

Mentha piperita (Peppermint) Leaf Oil, Olea Europaea

(Olive) Oil, Olus Oil (vegetable), Phenoxyethanol, Xanthan Gum

Uses

For temporary relief of minor aches and pains of muscles and joints associated with deep muscle therapy treatments.

DOSAGE AND ADMINISTRATION

Adults and children 12 years of age and older, apply to affected area no more than 10 times a day or as directed by your physical or occupational therapist.